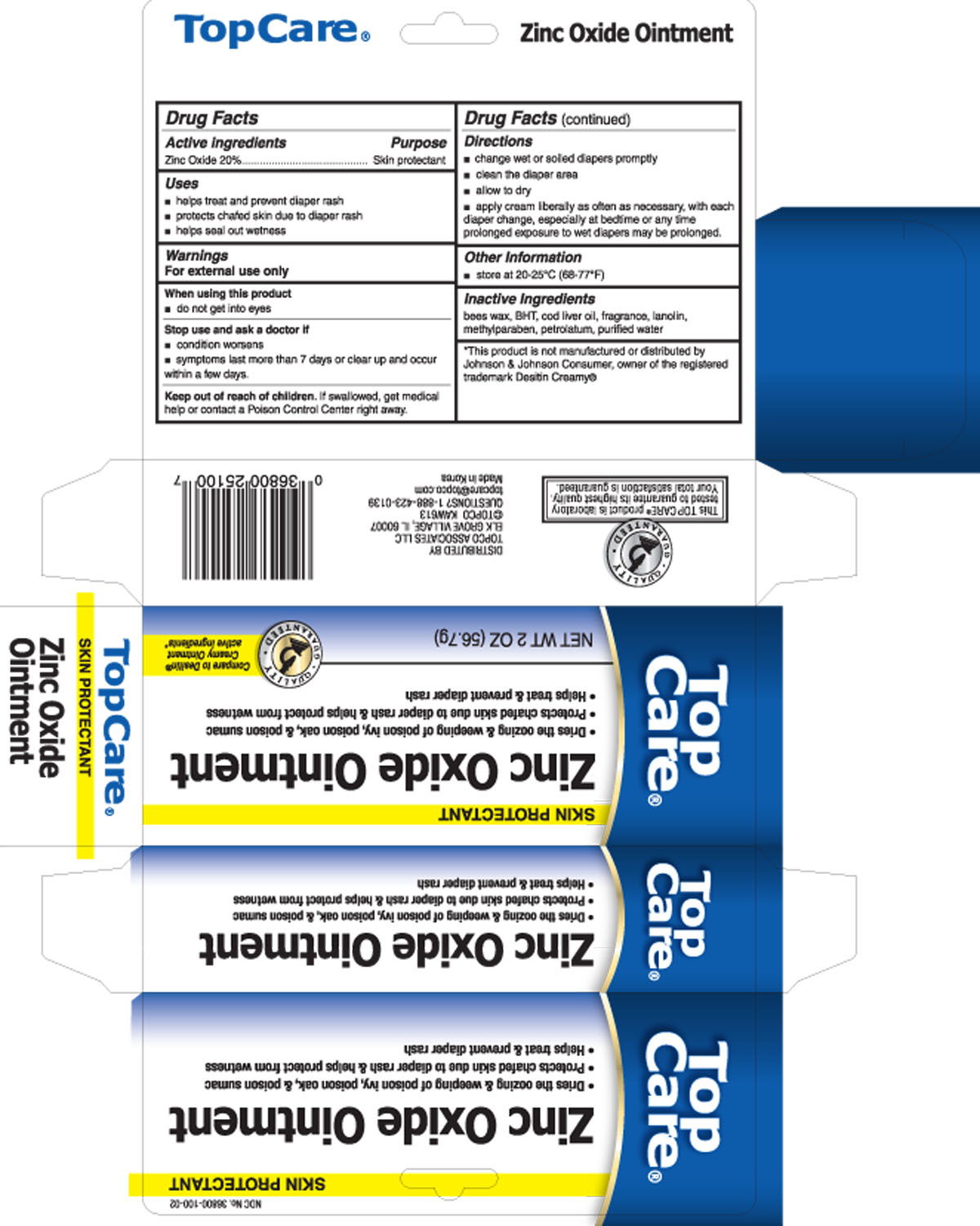 DRUG LABEL: Zinc Oxide
NDC: 36800-100 | Form: OINTMENT
Manufacturer: Topco Associates LLC
Category: otc | Type: HUMAN OTC DRUG LABEL
Date: 20130729

ACTIVE INGREDIENTS: ZINC OXIDE 20 g/100 g
INACTIVE INGREDIENTS: COD LIVER OIL; LANOLIN; METHYLPARABEN; PETROLATUM; WATER

Drug Facts

Active Ingredient

Zinc Oxide 20%

Purpose

Skin Protectant

Uses

- helps treat and prevent diaper rash
- protects chafed skin due to diaper rash
- helps seal out wetness

WARNINGS

For external use only.

When using this product

- do not get into eyes

Stop use and ask a doctor if

- condition worsens
- symptoms last more than 7 days or clear up and occur within a few days.

Keep out of reach of children.

If swallowed, get medical help or contact a Poison Control Center right away.

Directions

- change wet or soiled diapers promptly
- clean the diaper area
- allow to dry
- apply cream liberally as often as necessary, with each diaper change, especially at bedtime or any time prolonged exposure to wet diapers may be prolonged.

Other Information

- store at 20-25°C (68-77°F)

Inactive Ingredients

bees wax, BHT, cod liver oil, fragrance, lanolin, methylparaben, petrolatum, purified water